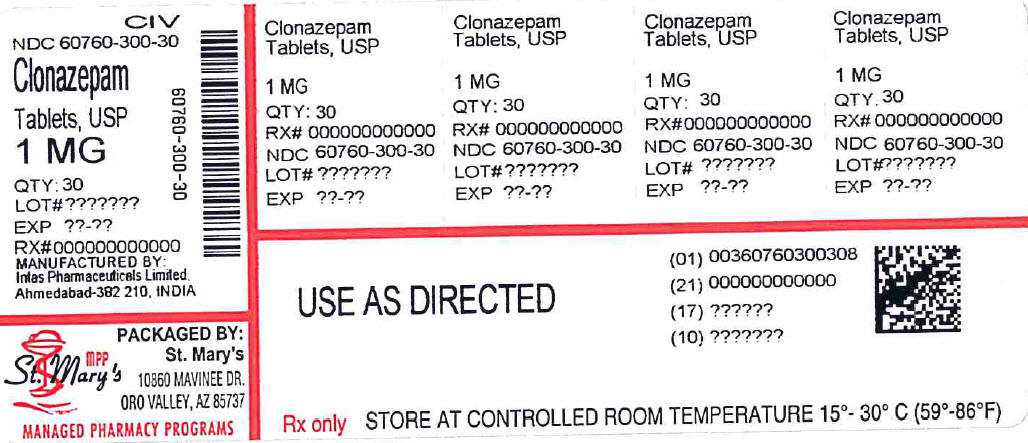 DRUG LABEL: Clonazepam
NDC: 60760-300 | Form: TABLET
Manufacturer: St Marys Medical Park Pharmacy
Category: prescription | Type: HUMAN PRESCRIPTION DRUG LABEL
Date: 20250522
DEA Schedule: CIV

ACTIVE INGREDIENTS: CLONAZEPAM 1 mg/1 1
INACTIVE INGREDIENTS: ANHYDROUS LACTOSE; LACTOSE MONOHYDRATE; MAGNESIUM STEARATE; CELLULOSE, MICROCRYSTALLINE; STARCH, CORN; FD&C BLUE NO. 2

Clonazepam Tablets, USP
CIV
Rx only,

CONTRAINDICATIONS

Clonazepam should not be used in patients with a history of sensitivity to benzodiazepines, nor in patients with clinical or biochemical evidence of significant liver disease. It may be used in patients with open angle glaucoma who are receiving appropriate therapy but is contraindicated in acute narrow angle glaucoma.

ADVERSE REACTIONS

The adverse experiences for clonazepam are provided separately for patients with seizure disorders and with panic disorder.

DOSAGE AND ADMINISTRATION

Clonazepam is available as a tablet. The tablets should be administered with water by swallowing the tablet whole.

HOW SUPPLIED

Clonazepam tablets USP 1 mg are blue, round, flat faced, beveled edge, debossed with “C 1” on one side and plain on the other. They are supplied as follows:

NDC: 60760-300-30 bottle of 30

Store at 25°C (77°F); excursions permitted to 15° to 30°C (59° to 86°F). [See USP Controlled Room Temperature].

Medication Guide
Clonazepam Tablets, USP
CIV

Read this Medication Guide before you start taking clonazepam tablets and each time you get a refill. There may be new information. This information does not take the place of talking to your healthcare provider about your medical condition or treatment.

Clonazepam tablets can cause serious side effects. Because stopping clonazepam tablets suddenly can also cause serious problems, do not stop taking clonazepam tablets without talking to your healthcare provider first.

What is the most important information I should know about clonazepam tablets?

Do not stop taking clonazepam tablets without first talking to your healthcare provider.

Stopping clonazepam tablets suddenly can cause serious problems.

Clonazepam tablets can cause serious side effects, including:

1. Clonazepam tablets can slow your thinking and motor skills
  - Do not drive, operate heavy machinery, or do other dangerous activities until you know how clonazepam tablets affects you.
  - Do not drink alcohol or take other drugs that may make you sleepy or dizzy while taking clonazepam until you talk to your healthcare provider. When taken with alcohol or drugs that cause sleepiness or dizziness, clonazepam tablets may make your sleepiness or dizziness worse.
2. Like other antiepileptic drugs, clonazepam tablets may cause suicidal thoughts or actions in a very small number of people, about 1 in 500.
  Call a healthcare provider right away if you have any of these symptoms, especially if they are new, worse, or worry you:
  - thoughts about suicide or dying
  - attempt to commit suicide
  - new or worse depression
  - new or worse anxiety
  - feeling agitated or restless
  - panic attacks
  - trouble sleeping (insomnia)
  - new or worse irritability
  - acting aggressive, being angry, or violent
  - acting on dangerous impulses
  - an extreme increase in activity and talking (mania)
  - other unusual changes in behavior or mood
  How can I watch for early symptoms of suicidal thoughts and actions?
  - Pay attention to any changes, especially sudden changes, in mood, behaviors, thoughts, or feelings.
  - Keep all follow-up visits with your healthcare provider as scheduled.
  Call your healthcare provider between visits as needed, especially if you are worried about symptoms.
  Suicidal thoughts or actions can be caused by things other than medicines. If you have suicidal thoughts or actions, your healthcare provider may check for other causes.
  Do not stop clonazepam tablets without first talking to a healthcare provider.
  Stopping clonazepam tablets suddenly can cause serious problems. Stopping clonazepam tablets suddenly can cause seizures that will not stop (status epilepticus).
3. Clonazepam tablets may harm your unborn or developing baby.
  - If you take clonazepam tablets during pregnancy, your baby is at risk for serious birth defects. These defects can happen as early as in the first month of pregnancy, even before you know you are pregnant. Birth defects may occur even in children born to women who are not taking any medicines and do not have other risk factors.
  - Children born to mothers receiving benzodiazepine medications (including clonazepam tablets) late in pregnancy may be at some risk of experiencing breathing problems, feeding problems, hypothermia, and withdrawal symptoms.
  - Tell your healthcare provider right away if you become pregnant while taking clonazepam tablets. You and your healthcare provider should decide if you will take clonazepam tablets while you are pregnant.
  - If you become pregnant while taking clonazepam tablets, talk to your healthcare provider about registering with the North American Antiepileptic Drug Pregnancy Registry. You can register by calling 1-888-233-2334. The purpose of this registry is to collect information about the safety of antiepileptic drugs during pregnancy.
  - Clonazepam tablets can pass into breast milk. Talk to your healthcare provider about the best way to feed your baby if you take clonazepam tablets. You and your healthcare provider should decide if you will take clonazepam tablets or breast feed. You should not do both.
4. Clonazepam tablets can cause abuse and dependence.
  - Do not stop taking clonazepam tablets all of a sudden. Stopping clonazepam tablets suddenly can cause seizures that do not stop, hearing or seeing things that are not there (hallucinations), shaking, and stomach and muscle cramps.
    - Talk to your doctor about slowly stopping clonazepam tablets to avoid getting sick with withdrawal symptoms.
    - Physical dependence is not the same as drug addiction. Your healthcare provider can tell you more about the differences between physical dependence and drug addiction.

Clonazepam tablets are a federally controlled substance (C-IV) because it can be abused or lead to dependence. Keep clonazepam tablets in a safe place to prevent misuse and abuse. Selling or giving away clonazepam tablets may harm others, and is against the law. Tell your doctor if you have ever abused or been dependent on alcohol, prescription medicines or street drugs.

What is a clonazepam tablet?

Clonazepam tablet is a prescription medicine used alone or with other medicines to treat:

- certain types of seizure disorders (epilepsy) in adults and children
- panic disorder with or without fear of open spaces (agoraphobia) in adults

It is not known if clonazepam tablet is safe or effective in treating panic disorder in children younger than 18 years old.

Who should not take clonazepam tablets?

Do not take clonazepam tablets if you:

- are allergic to benzodiazepines
- have significant liver disease
- have an eye disease called acute narrow angle glaucoma

Ask your healthcare provider if you are not sure if you have any of the problems listed above.

What should I tell my healthcare provider before taking clonazepam tablets?

Before you take clonazepam tablets, tell your healthcare provider if you:

- have liver or kidney problems
- have lung problems (respiratory disease)
- have or have had depression, mood problems, or suicidal thoughts or behavior
- have any other medical conditions

Tell your healthcare provider about all the medicines you take, including prescription and non-prescription medicines, vitamins, and herbal supplements. Taking clonazepam tablets with certain other medicines can cause side effects or affect how well they work. Do not start or stop other medicines without talking to your healthcare provider.

Know the medicines you take. Keep a list of them and show it to your healthcare provider and pharmacist when you get a new medicine.

How should I take clonazepam tablets?

- Take clonazepam tablets exactly as your healthcare provider tells you. Clonazepam is available as a tablet.
- Do not stop taking clonazepam tablets without first talking to your healthcare provider.
  Stopping clonazepam tablets suddenly can cause serious problems.
- Clonazepam tablets should be taken with water and swallowed whole.
- If you take too much clonazepam tablets, call your healthcare provider or local Poison Control Center right away.

What should I avoid while taking clonazepam tablets?

- Clonazepam tablets can slow your thinking and motor skills. Do not drive, operate heavy machinery, or do other dangerous activities until you know how clonazepam tablets affects you.
- Do not drink alcohol or take other drugs that may make you sleepy or dizzy while taking clonazepam until you talk to your healthcare provider. When taken with alcohol or drugs that cause sleepiness or dizziness, clonazepam tablets may make your sleepiness or dizziness worse.

What are the possible side effects of clonazepam tablets?

See “What is the most important information I should know about clonazepam tablets?”

Clonazepam tablets can also make your seizures happen more often or make them worse. Call your healthcare provider right away if your seizures get worse while taking clonazepam tablets.

The most common side effects of clonazepam tablets include:

- Drowsiness
- Problems with walking and coordination
- Dizziness
- Depression
- Fatigue
- Problems with memory

These are not all the possible side effects of clonazepam tablets. For more information, ask your healthcare provider or pharmacist.

Tell your healthcare provider if you have any side effect that bothers you or that does not go away.

Call your doctor for medical advice about side effects. You may report side effects to FDA at 1-800-FDA-1088.

How should I store clonazepam tablets?

- Store clonazepam tablets between 59ºF to 86ºF (15ºC to 30ºC).

Keep clonazepam tablets and all medicines out of the reach of children.

General Information about clonazepam tablets

Medicines are sometimes prescribed for purposes other than those listed in a Medication Guide. Do not use clonazepam tablets for a condition for which it was not prescribed. Do not give clonazepam tablets to other people, even if they have the same symptoms that you have. It may harm them.

This Medication Guide summarizes the most important information about clonazepam tablets. If you would like more information, talk with your healthcare provider. You can ask your pharmacist or healthcare provider for information about clonazepam tablets that is written for health professionals.

What are the ingredients in clonazepam tablets?

Active Ingredient: clonazepam

Inactive Ingredients:

- Tablets
  - 0.5 mg tablets contain anhydrous lactose, lactose monohydrate, magnesium stearate, microcrystalline cellulose, starch (corn) and FD&C Yellow No. 6 Lake.
  - 1 mg tablets contain anhydrous lactose, lactose monohydrate, magnesium stearate, microcrystalline cellulose, starch (corn) and FD&C Blue No. 2 Lake.
  - 2 mg tablets contain anhydrous lactose, lactose monohydrate, magnesium stearate, microcrystalline cellulose and starch (corn)

This Medication Guide has been approved by the U.S. Food and Drug Administration.

Manufactured For:
Accord Healthcare, Inc.,
1009, Slater Road,
Suite 210-B,
Durham, NC 27703,
USA.

Manufactured By:
Intas Pharmaceuticals Limited,
Plot No. : 457, 458,
Village – Matoda,
Bavla Road, Ta.- Sanand,
Dist.- Ahmedabad – 382 210.
India.

10 7744 1 626035

Issued October, 2010.